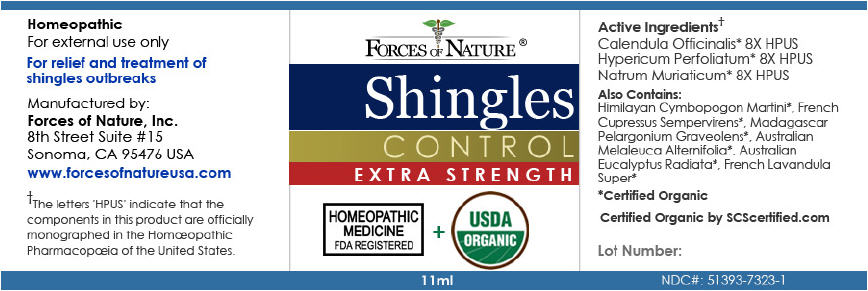 DRUG LABEL: Shingles Control 
NDC: 51393-7323 | Form: SOLUTION/ DROPS
Manufacturer: Forces of Nature
Category: homeopathic | Type: HUMAN OTC DRUG LABEL
Date: 20110331

ACTIVE INGREDIENTS: CALENDULA OFFICINALIS FLOWERING TOP 8 [hp_X]/1000 mL; HYPERICUM PERFORATUM 8 [hp_X]/1000 mL; SODIUM CHLORIDE 8 [hp_X]/1000 mL
INACTIVE INGREDIENTS: EUCALYPTUS OIL; TEA TREE OIL; LAVANDIN OIL; GERANIUM OIL, ALGERIAN TYPE; PALMAROSA OIL

Shingles Control
Extra Strength

Drug Facts

ACTIVE INGREDIENT

PURPOSE

Active Ingredients [The letters 'HPUS' indicate that the component(s) in this product is (are) officially monographed in the Homœopathic Pharmacopœia of the United States.] Equal parts of: | Purpose
Calendula Officinalis 8X HPUS | Promotes healthy skin
Natrum Muriaticum 8X HPUS | Remedy for herpes, skin eruptions, hives
Hypericum Perforatum 8X HPUS | For herpes zoster/shingles

Also Includes

Certified Organic Oils of: Eucalypus Radiata Leaf, French Lavandin Super, Napalese Palmarosa, Tea Tree, Pelargonium Graveolens Leaf, Cypress

Directions

Apply to affected area at first sign of an outbreak 3-5 times per day. Avoid contact with eyes.

Indications

For relief and treatment of skin inflammation, pain and redness of shingles outbreaks.

Warnings

Product Note: Shingles is a viral infection (herpes zoster) of the skin with symptoms of rashes or blisters, redness and pain. Viral infections are often highly contagious.

ASK DOCTOR

If skin symptoms worsen consult a health care professional.

STOP USE

Some individuals may be sensitive to tea tree or other oils. Begin with a small drop to determine if the product causes any increased redness or irritation and discontinue use if it irritates your skin.

PREGNANCY OR BREAST FEEDING

If you are pregnant or breast-feeding, ask a health professional before use.

Keep out of the reach of children.

DO NOT USE

External use only. If accidental ingestion, get medical help or contact a Poison Control Center.

Do not apply to the eyes or mucous membranes.

KEEP OUT OF REACH OF CHILDREN

Keep all medicines out of the reach of children.

Stop use and ask a doctor if condition worsens or symptoms last more than 7 days or clear up and occur again within a few days.

PRINCIPAL DISPLAY PANEL - 11ml Bottle Label

FORCES OF NATURE ®

Shingles
CONTROL
EXTRA STRENGTH

HOMEOPATHIC
MEDICINE
FDA REGISTERED
+
USDA
ORGANIC

11ml